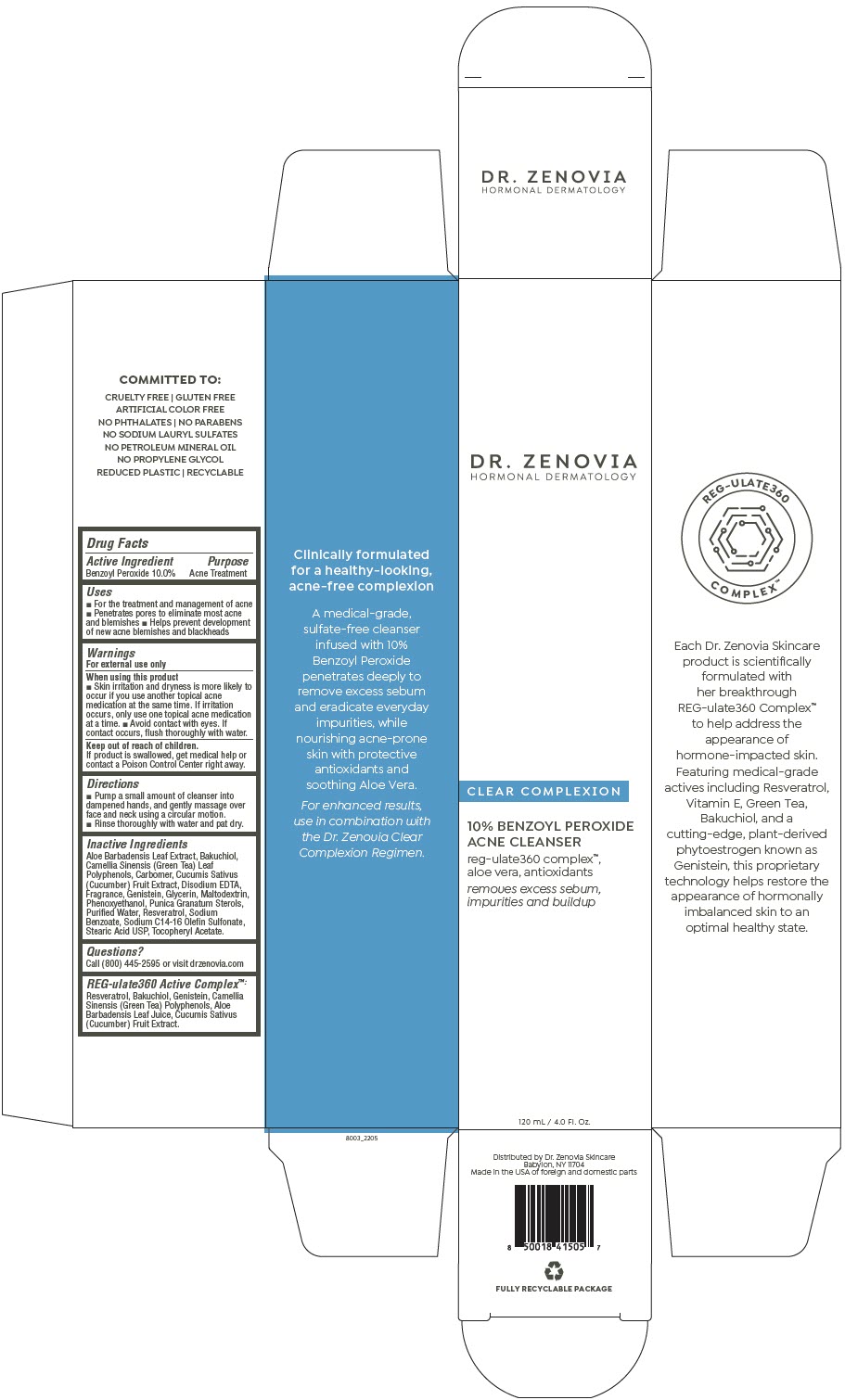 DRUG LABEL: Dr. Zenovia  Acne Cleanser
NDC: 51326-803 | Form: LIQUID
Manufacturer: Topiderm, Inc.
Category: otc | Type: HUMAN OTC DRUG LABEL
Date: 20240611

ACTIVE INGREDIENTS: BENZOYL PEROXIDE 100 mg/1 mL
INACTIVE INGREDIENTS: ALOE VERA LEAF; BAKUCHIOL; GREEN TEA LEAF; CARBOMER COPOLYMER TYPE A (ALLYL PENTAERYTHRITOL CROSSLINKED); CUCUMBER JUICE; EDETATE DISODIUM; GLYCERIN; MALTODEXTRIN; PHENOXYETHANOL; PUNICA GRANATUM STEROLS; WATER; RESVERATROL; SODIUM BENZOATE; SODIUM C14-16 OLEFIN SULFONATE; GENISTEIN; STEARIC ACID; .ALPHA.-TOCOPHEROL ACETATE, DL-

Dr. Zenovia Acne Cleanser

Drug Facts

Active Ingredient

Benzoyl Peroxide 10.0%

Purpose

Acne Treatment

Uses

- For the treatment and management of acne
- Penetrates pores to eliminate most acne and blemishes
- Helps prevent development of new acne blemishes and blackheads

Warnings

For external use only

When using this product

- Skin irritation and dryness is more likely to occur if you use another topical acne medication at the same time. If irritation occurs, only use one topical acne medication at a time.
- Avoid contact with eyes. If contact occurs, flush thoroughly with water.

Keep out of reach of children.

If product is swallowed, get medical help or contact a Poison Control Center right away.

Directions

- Pump a small amount of cleanser into dampened hands, and gently massage over face and neck using a circular motion.
- Rinse thoroughly with water and pat dry.

Inactive Ingredients

Aloe Barbadensis Leaf Extract, Bakuchiol, Camellia Sinensis (Green Tea) Leaf Polyphenols, Carbomer, Cucumis Sativus (Cucumber) Fruit Extract, Disodium EDTA, Fragrance, Genistein, Glycerin, Maltodextrin, Phenoxyethanol, Punica Granatum Sterols, Purified Water, Resveratrol, Sodium Benzoate, Sodium C14-16 Olefin Sulfonate, Stearic Acid USP, Tocopheryl Acetate.

Questions?

Call (800) 445-2595 or visit drzenovia.com

REG-ulate360 Active Complex™

Resveratrol, Bakuchiol, Genistein, Camellia Sinensis (Green Tea) Polyphenols, Aloe Barbadensis Leaf Juice, Cucumis Sativus (Cucumber) Fruit Extract.

Distributed by Dr. Zenovia Skincare
Babylon, NY 11704

PRINCIPAL DISPLAY PANEL - 120 mL Bottle Carton

DR. ZENOVIA
HORMONAL DERMATOLOGY

CLEAR COMPLEXION

10% BENZOYL PEROXIDE
ACNE CLEANSER

reg-ulate360 complex™,
aloe vera, antioxidants

removes excess sebum,
impurities and buildup

120 mL / 4.0 Fl. Oz.